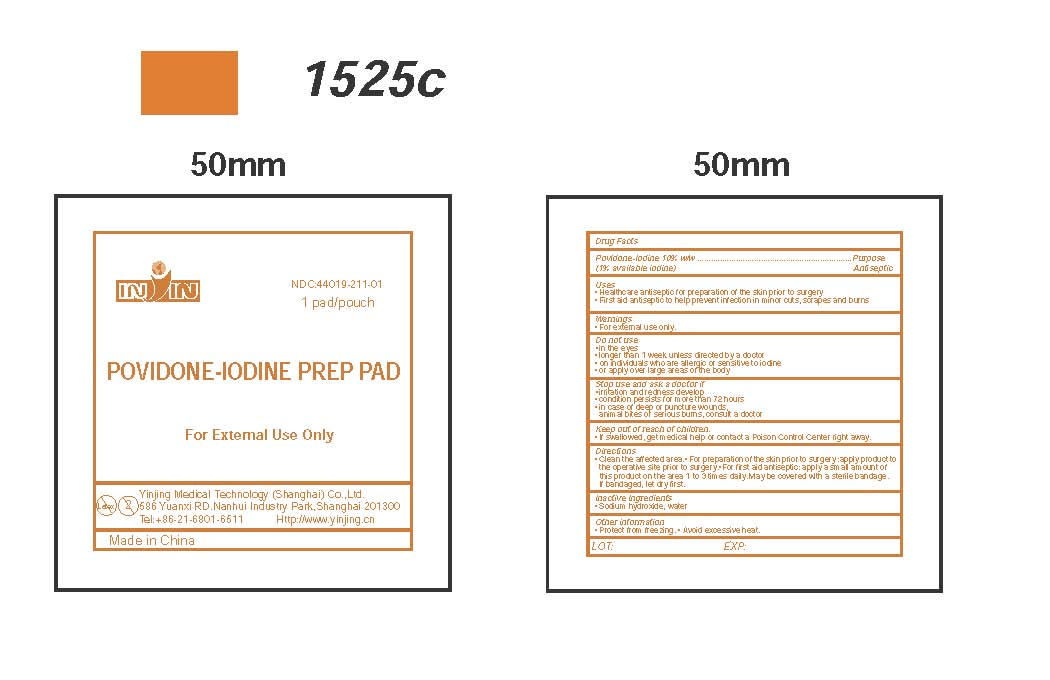 DRUG LABEL: POVIDONE-IODINE PREP PAD

NDC: 44019-211 | Form: SWAB
Manufacturer: Yinjing Medical Technology (Shanghai) Co., Ltd.
Category: otc | Type: HUMAN OTC DRUG LABEL
Date: 20171227

ACTIVE INGREDIENTS: POVIDONE-IODINE 10 g/100 g
INACTIVE INGREDIENTS: SODIUM HYDROXIDE; WATER

POVIDONE-IODINE PREP PAD

Active Ingredients

Povidone-Iodine 10% w/w
(1% titratable iodine)

Purpose

Antiseptic

Use

First aid antiseptic to help prevent infection in scrapes, minor cuts and burns Antiseptic to prepare skin prior to surgery. Uses antiseptic skin preparation

Stop Use Section

Stop use and ask a doctor if skin irritation, redness, swelling, or pain occurs.

Warnings Section

Warnings • Do not use if allergic to iodine • For external use only • Do not use in eyes • Avoid pooling beneath patient • In case of accidental ingestion, seek professional assistance or consult a poison control center immediately.

Keep Out of Reach of Children Section

Keep out of reach of children.

Directions Section

Directions apply locally as needed

Inactive Ingredients Section

Inactive ingredients Sodium hydroxide, water

Other Information Section

Other information
For Hospital or Professional Use Only.
Store at room temperature: 15℃- 30 ℃

Shanghai Yinjing Medical Supplies Co., Ltd.
No.586 Yuanxi RD.Nanhui Industry Park,Shanghai 201300
Tel:+86-21-68016633 Http://www.yinjing.cn
Made in China
LOT EXP.

PACKAGE LABEL

inin
NDC:44019-211-01
1 pad/pouch
POVIDONE-IODINE PREP PAD
For External Use Only